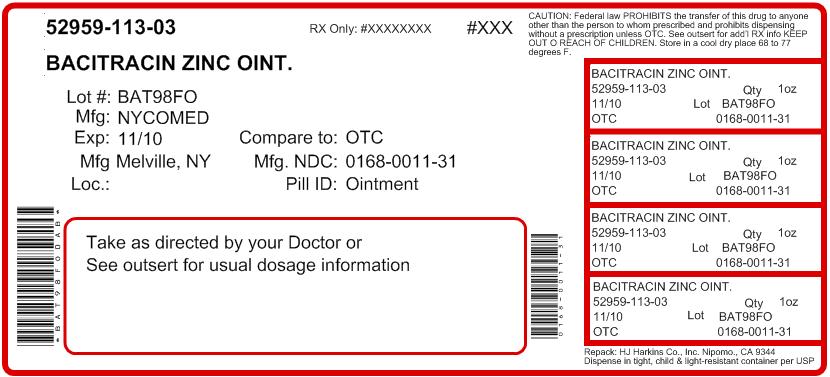 DRUG LABEL: Bacitracin Zinc
NDC: 52959-113 | Form: OINTMENT
Manufacturer: H.J. Harkins Company, Inc.
Category: otc | Type: HUMAN OTC DRUG LABEL
Date: 20110819

ACTIVE INGREDIENTS: Bacitracin Zinc 500 [USP'U]/1 g
INACTIVE INGREDIENTS: petrolatum

Bacitracin Zinc Ointment USP

Active ingredients (in each gram)

Bacitracin Zinc (equal to 500 bacitracin units)

Purpose

Antibiotic

INDICATIONS AND USAGE

Uses first aid to help prevent infection in minor cuts scrapes burns

Warnings For External use only

Do not use in the eyes over large areas of the body if you are allergic to any of the ingredients

Ask a doctor before use in case of deep or puncture wounds, animal bites or serious burns

When using this product do not use longer than 1 week unless directed by a doctor

Stop use and ask a doctor if the condition persists or gets worse if a rash or other allergic reaction develops

Keep out of reach of children. If swallowed, get medical help or contact a Poison Control Center right away.

DOSAGE AND ADMINISTRATION

Directions clean the affected area apply a small amount of this product (an amount equal to the surface area of the tip of A finger) on the area 1 to 3 times daily may be covered with a sterile bandage

Other information store at room temperature

Inactive ingredient white petrolatum

QUESTIONS

E. FOUGERA and CO.
a division of Nycomed US Inc.
MELVILLE, NEW YORK 11747
Repacked by:
H.J. Harkins Company Inc.
Nipomo, CA 93444